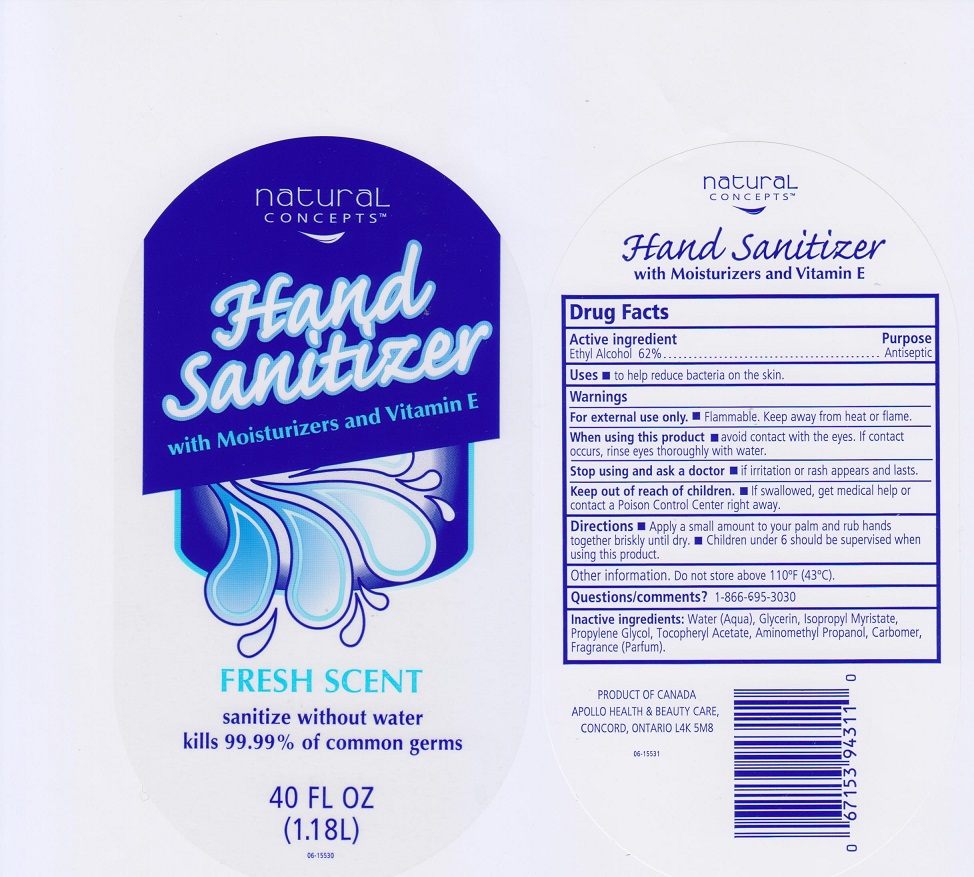 DRUG LABEL: Natural Concepts Hand Sanitizer with Moisturizers and Vitamin E
NDC: 63148-224 | Form: GEL
Manufacturer: Apollo Health and Beauty Care Inc.
Category: otc | Type: HUMAN OTC DRUG LABEL
Date: 20200316

ACTIVE INGREDIENTS: ALCOHOL 620 mg/1 mL
INACTIVE INGREDIENTS: WATER; GLYCERIN; ISOPROPYL MYRISTATE; PROPYLENE GLYCOL; .ALPHA.-TOCOPHEROL ACETATE, DL-; AMINOMETHYLPROPANOL; CARBOMER 934

Drug Facts

Active ingredient

Ethyl Alcohol 62%

Purpose

Antiseptic

Uses

- to help reduce bacteria on the skin.

Warnings

For external use only

- Flammable. Keep away from heat or flame.

When using thi sproduct

- avoid contact with the eyes. If contact occurs, rinse eyes thoroughly with water.

Stop useing and ask a doctor if

- irritation or rash appears and lasts.

Keep out of reach of children.

- If swallowed, get medical help or contact a Poison Control Center right away.

Directions

- Apply a small amount to your palm and rub hands together briskly until dry.
- Children under 6 should be supervised when using this product.

Other information

Do not store above 110°F (43°C)

Questions / comments?

1-866-695-3030

Inactive ingredients

Water (Aqua), Glycerin, Isopropyl Myristate, Propylene Glycol, Tocopheryl Acetate, Aminomethyl Propanol, Carbomer, Fragrance (Parfum).